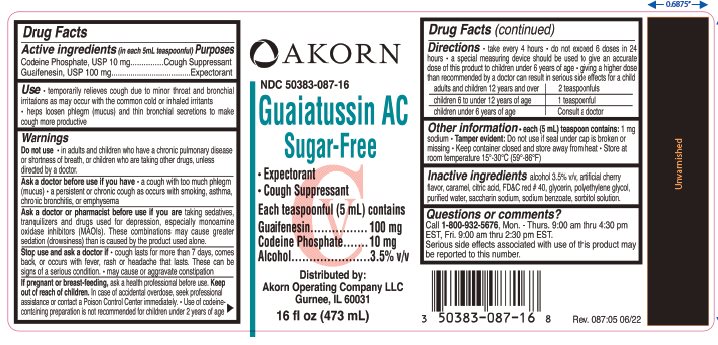 DRUG LABEL: Guaiatussin AC
NDC: 50383-087 | Form: LIQUID
Manufacturer: Akorn Operating Company LLC
Category: otc | Type: HUMAN OTC DRUG LABEL
Date: 20221014
DEA Schedule: CV

ACTIVE INGREDIENTS: CODEINE PHOSPHATE 10 mg/5 mL; GUAIFENESIN 100 mg/5 mL
INACTIVE INGREDIENTS: ALCOHOL; CARAMEL; ANHYDROUS CITRIC ACID; FD&C RED NO. 40; GLYCERIN; POLYETHYLENE GLYCOL 4000; WATER; SACCHARIN SODIUM; SODIUM BENZOATE; SORBITOL

Drug Facts

Active ingredients (in each 5 mL teaspoonful)

Codeine Phosphate, USP 10 mg

Guaifenesin, USP 100 mg

Purposes

Cough Suppressant

Expectorant

Uses

- temporarily relieves cough due to minor throat and bronchial irritations as may occur with the common cold or inhaled irritants
- helps loosen phlegm (mucus) and thin bronchial secretions to make cough more productive

Warnings

Do not use

- in adults and children who have a chronic pulmonary disease or shortness of breath, or children who are taking other drugs, unless directed by a doctor

Ask a doctor before use if you have

- a cough with too much phlegm (mucus)
- a persistent or chronic cough as occurs with smoking, asthma, chronic bronchitis, or emphysema

Ask a doctor or pharmacist before use if you are

taking sedatives, tranquilizers and drugs used for depression, especially monoamine oxidase inhibitors (MAOIs). These combinations may cause greater sedation (drowsiness) than is caused by the product used alone.

Stop use and ask a doctor if

- cough lasts more than 7 days, comes back, or occurs with fever, rash or headache that lasts. These can be signs of a serious condition.
- may cause or aggravate constipation

If pregnant or breast-feeding

ask a health professional before use.

Keep Out of Reach of Children

In case of accidental overdose, seek professional assistance or contact a Poison Control Center immediately.

- Use of codeine-containing preparations is not recommended for children under 2 years of age

Directions

- take every 4 hours
- do not exceed 6 doses in 24 hours
- a special measuring device should be used to give an accurate dose of this product to children under 6 years of age
- giving a higher dose than recommended by a doctor can result in serious side effects for a child

adults and children 12 years and over | 2 teaspoonfuls
children 6 to under 12 years of age | 1 teaspoonfuls
children under 6 years of age | Consult a doctor

Other information

- each (5 mL) teaspoon contains: 1 mg sodium
- Tamper evident: Do not use if seal under cap is broken or missing.
- Keep container closed and away from heat.
- Store at room temperature 15°- 30°C (59°-86°F)

Inactive Ingredients

alcohol 3.5% v/v, artificial cherry flavor, caramel, citric acid, FD&C red # 40, glycerin, polyethylene glycol, purified water, saccharin sodium, sodium benzoate, sorbitol solution.

Questions or comments?

Call 1-800-932-5676, Mon.-Thurs 9:00 am thru 4:30 pm EST, Fri. 9:00 am thru 2:30 pm EST.

Serious side effects associated with use of this product may be reported to this number.

Package/Label Principal Display Panel

AKORN

NDC 50383-087-16

Guaiatussin AC

Sugar-Free

- Expectorant
- Cough Suppresant

Each teaspoonful (5 mL) contains

Guaifenesin ……………. 100 mg

Codeine Phosphate…….. 10 mg

Alcohol………………….... 3.5% v/v

Distributed by:

Akorn Operating Company LLC

Gurnee, IL 60031

16 fl oz (473 mL)